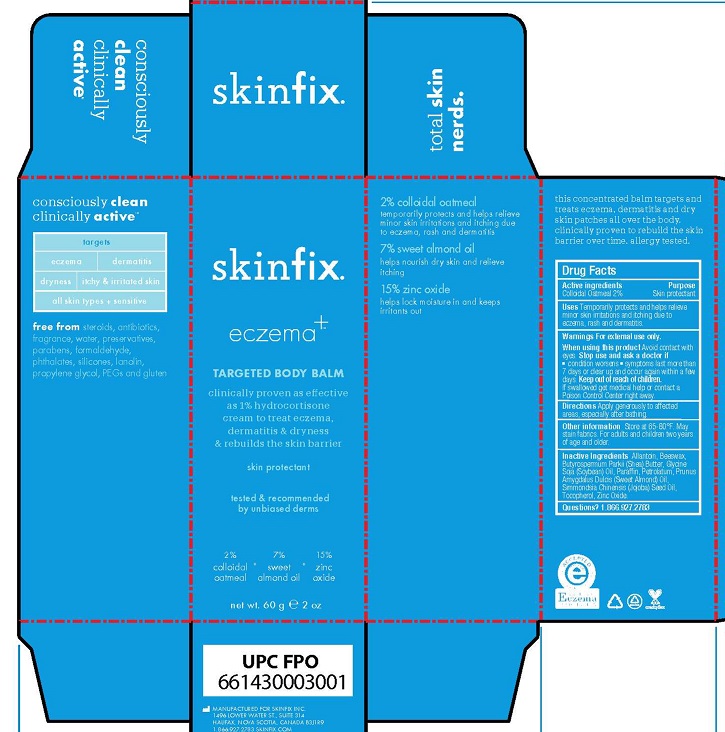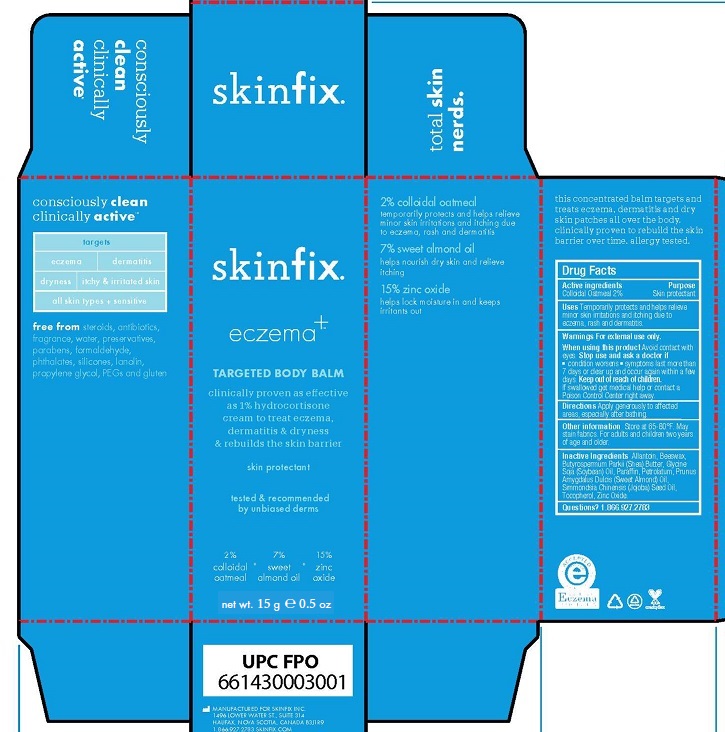 DRUG LABEL: TARGETED BODY BALM
NDC: 61328-122 | Form: OINTMENT
Manufacturer: Skinfix, Inc.
Category: otc | Type: HUMAN OTC DRUG LABEL
Date: 20221224

ACTIVE INGREDIENTS: OATMEAL 2 g/100 g
INACTIVE INGREDIENTS: ALLANTOIN; YELLOW WAX; SHEANUT OIL; SOYBEAN OIL; PARAFFIN; PETROLATUM; ALMOND OIL; JOJOBA OIL; TOCOPHEROL; ZINC OXIDE

SKINFIX - ECZEMA+ TARGETED BODY BALM (61328-122)

Active Ingredients

Colloidal Oatmeal 2%

Purpose

Skin protectant

Uses

Temporarily protects and helps relieve minor skin irritations and itching due to eczema, rash and dermatitis.

Warnings

For external use only.

When using this product

- Avoid contact with eyes

Stop use and ask a doctor if

- condition worsens
- symptoms last more than 7 days or clear up and occur again within a few days

Keep out of reach of children. If swallowed get medical help or contact a Poison Control Center right away.

Directions

Apply as needed.

Other Information

Store at 65-80°F. May stain fabrics. For adults and children two years of age and older.

Inactive Ingredients

Allantoin, Beeswax, Butyrospermum Parkii (Shea) Butter, Glycine Soja (Soybean) Oil, Paraffin Wax, Petrolatum, Prunus Amygdalus (Sweet Almond) Oil, Simmondsia Chinensis (Jojoba) Seed Oil, Tocopherol, Zinc Oxide.

PACKAGE LABEL

15 g

60g